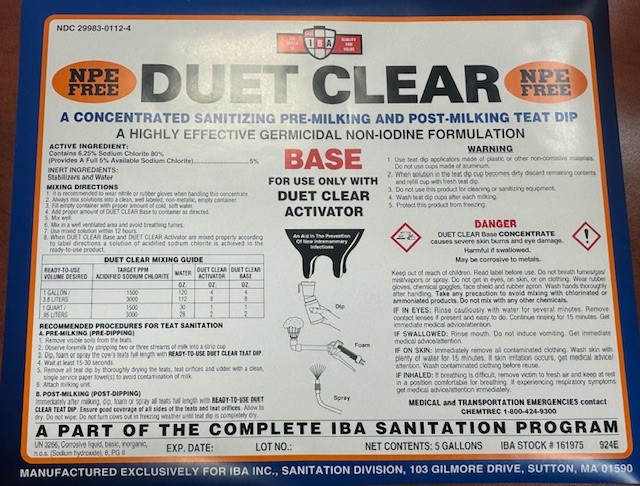 DRUG LABEL: DUET CLEAR BASE
NDC: 29983-0112 | Form: SOLUTION
Manufacturer: IBA
Category: animal | Type: OTC ANIMAL DRUG LABEL
Date: 20240918

ACTIVE INGREDIENTS: SODIUM CHLORITE 5 g/1 L

DUET CLEAR A CONCENTRATED SANITIZING PRE-MILKING AND POST MILKING TEAT DIP A HIGHLY EFFECTIVE GERMICIDAL NON-IODINE FORMULATION

ACTIVE INGREDIENT

Contains 6.25% Sodium Chlorite 80%

(PROVIDES A FULL 5% AVAILABLE SODIUM CHLORITE)...........5%

INDICATIONS AND USAGE

MIXING DIRECTIONS

1. It is recommended to wear nitrile or rubber gloves when handling this concentrate to avoid staining hands.

2. Always mix solutions into a clean, well labeled, non-metalic, empty container.

3. Fill empty container with proper amount of cold, soft water.

4. Add proper amount of DUETC CLEAR Base to container as directed.

5. Add proper amount of DUET CLEAR Activator to container as directed. Mix until the color is uniform throughout.

6. Mix in a well ventilated area and avoid breathing fumes.

7. Use mixed solution within 12 hours.

8. When DUET CLEAR BASE and DUET CLEAR ACTIVATOR are mixed properly according to label directions a solution of acidified sodium chlorite is achieved in the ready-to-use product.

RECOMMENDED PROCEDURES FOR TEAT SANITATION

A. PRE-MILKING (PRE-DIPPING)

1. Remove visible soils from the teats.

2. Observe foremilk by strippping two or three streams of milk into a strip cup.

3. Dip or Spray the cow's teats full lenth with READY-TO-USE DUET CLEAR TEAT DIP.

4. Waut at least 15-30 seconds

5. Remove all teat dip by thoroughly drying the teats, teat orifices and udder with a clean, single service paper towel(s) to avoid contamination of milk.

6, Attach milking unit
POST-MILKING (POST DIPPING)

Immediately after milking, dip or spray all teats full length with READY-TO-USE DUET CLEAR TEAT DIP. Ensure good coverage of all sides of the teats and teat orifices. Allow to dry. Do not wipe. Do not turn cows out in freezing weather until teat dip is completely dry.

WARNING

1. Use teat dip applicators made of plastic or other non-corrosive materials. Do not use cups made of aluminum.

2.When solution in the teat dip cup becomes dirty discard remaining contents and refill cup with fresh teat dip.

3. Do not use this product for cleaning or sanitizing equipment.

4. Wash teat dip cups after each milking.

5. Protect this product from freezing.

FIRST AID PROCEDURES

Keep out of reachof children. Read label before use. Do not breath fumes/gas/mist/vapors or spray. Do not get in eyes, on skin, or on clothing. Wear rubber gloves, chemical goggles, face shield and rubber apron. Wash hands thoroughly after handling. Take any precation to avoid mixing with chlorinated or ammoniated products. do not mix with any other chemicals.

IF IN EYES: RINSE CAUSTIOUSLY WITH FRESH,TEPID WATER FOR SEVERAL MINUTES.REMOVE CONTACT LENSES IF PRESENT AND EASY TO DO. CONTINUE RINSING FOR 15 MINUTES. GET IMMEDIATE MEDICAL ADVICE/ATTENTION.

IF ON SKIN: Immediately remove all contaminated clothing. Wash skin with plenty of water for 15 minutes. If skin irritation occurs, get medical advice/attention. Wash contaminated clothing before reuse.

IF SWALLOWED: DO NOT INDUCE VOMITING.NEVER GIVE ANYTHING BY MOUTH TO AN UNCONSCIOUS PERSON.DRINK LARGE AMOUNTS OF WATER. IF VOMITING OCCURS, KEEP AIRWAYS OPEN. KEEP HEAD LAWER THAN THE HIPS TO PREVENT ASPIRATION INTO THE LUNGS. GET IMMEDIATE MEDICAL ADVISE/ATTENTION.

IF INHALED: If breathing is difficult, remove victim to fresh air and keep at rest in a position comfortable for breathing. If experiencing respiratory symptoms get medical advice/attention immediately.

ALWAYS SEEK IMMEDIATE MEDICAL ATTENTION

FOR MEDICAL EMERGENCIES CALL 1-800-424-9300